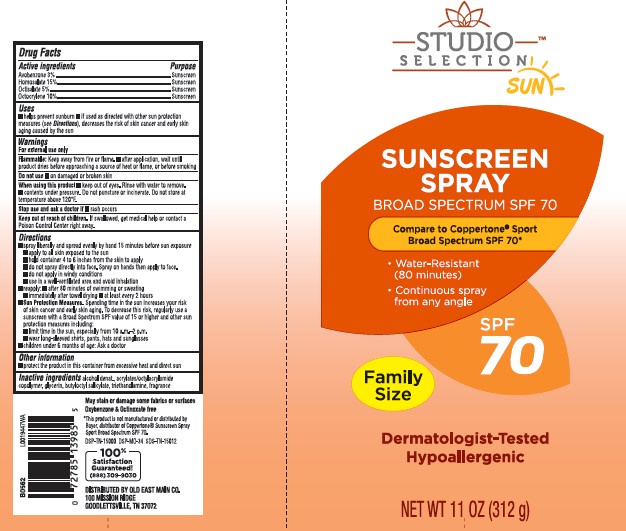 DRUG LABEL: Sunscreen
NDC: 55910-012 | Form: SPRAY
Manufacturer: Old East Main Co.
Category: otc | Type: HUMAN OTC DRUG LABEL
Date: 20260302

ACTIVE INGREDIENTS: AVOBENZONE 30 mg/1 g; HOMOSALATE 150 mg/1 g; OCTISALATE 50 mg/1 g; OCTOCRYLENE 100 mg/1 g
INACTIVE INGREDIENTS: ALCOHOL; ACRYLATE/ISOBUTYL METHACRYLATE/N-TERT-OCTYLACRYLAMIDE COPOLYMER (40000 MW); GLYCERIN; BUTYLOCTYL SALICYLATE; TROLAMINE

Studio Selection 958.000/958AA
Sport Sunscreen Spray SPF 70

active ingredients

Avobenzone 3%

Homosalate 15%

Octisalate 5%

Octocrylene 10%

Purpose

Sunscreen

uses

- helps prevent sunburn
- if used as directed with other skin protection measures (see Directions), decreases the risk of skin cancer and early skin aging caused by the sun.

Warnings

For external use only

Flammable

Keep away from fire or flame.

- after application, wait until product dries before approaching a souce of heat or flame, or before smoking

Do not use

On damaged or broken skin

When using this product

- Keep out of eyes. Rinse with water to remove.
- contents under pressure. Do not puncture or incinerate. Do not store at temperature above 120F.

stop use and ask a doctor

if rash occurs

Keep out of reach of children.

If swallowed, get medical help or contact a Poison Control Center right away.

directions

- spray liberally and spread evenly by hand 15 minutes before sun exposure.
- apply to all skin exposed to the sun
- do not spray directly into face. Spray on hands then apply to face.
- do not apply in windy conditions
- use in a well-ventilated area and avoid inhalation
- reapply after 80 minutes of swimming or sweating
- immediately after towel drying
- at least every 2 hours
- Sun protction Measures. Spending time in the sun increases your risk of skin cancer and early skin aging. To decrease this risk, regularly use a sunscreen with a Broad Spectrum SPF value of 15 or higher and other sun protection measures incluing:
- limit the time in the sun, especially from 10 a.m. - 2 p.m.
- wear long-sleeved shirts, pants, hats and sunglasses
- cildren under 6 month of age: Ask a doctor

Other information

- protect the product in the container from excessive heat and direct sun

inactive ingredients

alcohol denat., acrylates/octylacrylamide copolymer, glycerin, butyloctyl salicylate, triethanolamine, fragrance

claims

May stain or damage some fabrics or surfaces

Oxybenzone & Octinoxate free

disclaimer

*This product is not manufactured or distributed by Bayer, distributor of Coppertone®Sunscreen Spray Sport Broad Spectrum SPF 70.

ADVERSE REACTION

DISTRIBUTED BY OLD EAST MAIN CO.

100 MISSION RIDGE

GOODLETTSVILLE, TN 37072

100% Satisfaction Guaranteed!

(888)309-9030

DSP-TN-15000 DSP-MO-34 SDS-TN-15012

PRINCIPAL DISPLAY PANEL

STUDIO SELECTION™ SUN

SUNSCREEN SPRAY

BROAD SPECTRUM SPF 70

Compare to Coppertone®Sport Broad Spectrum SPF 70*

- Water-resistant (80 minutes
- Continuous spray from any angle

SPF 70

Family Size

Dermatologist-Tested

Hypoallergenic

NET WT 11 OZ (312 g)